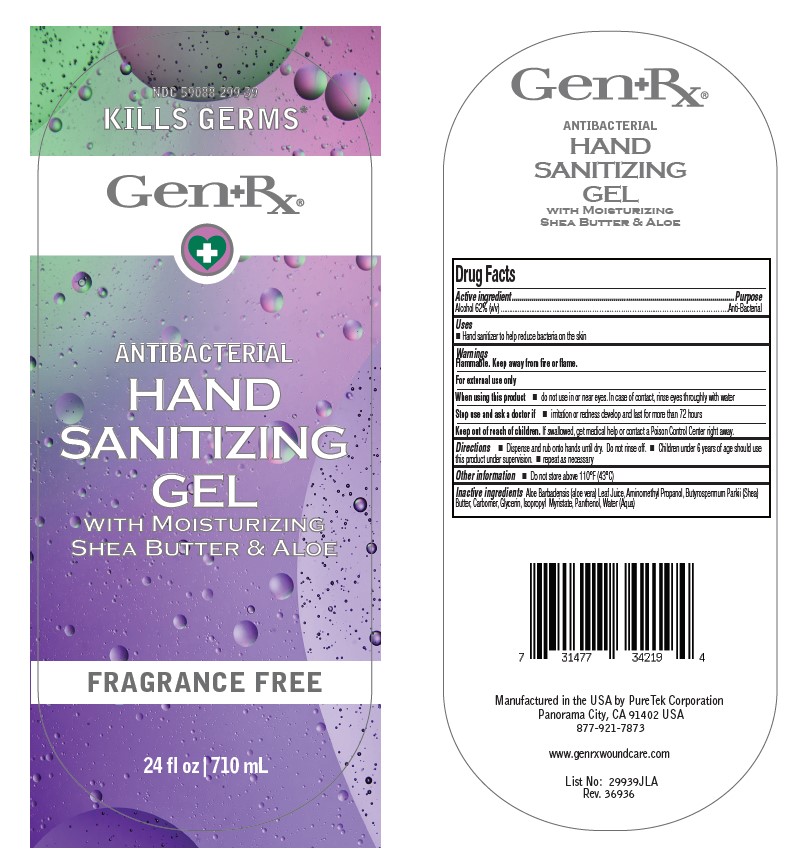 DRUG LABEL: GenRx Anti-Bacterial Gel
NDC: 59088-299 | Form: LIQUID
Manufacturer: PureTek Corporation
Category: otc | Type: HUMAN OTC DRUG LABEL
Date: 20241001

ACTIVE INGREDIENTS: ALCOHOL 62 mL/100 mL
INACTIVE INGREDIENTS: SHEA BUTTER; AMINOMETHYL PROPANEDIOL; ALOE VERA LEAF; GLYCERIN; CARBOMER HOMOPOLYMER TYPE C; ISOPROPYL MYRISTATE; PANTHENOL; WATER

GENRX unfragranced ANTI-BACTERIAL GEL- alcohol liquid

Active Ingredient

Alcohol 62% (v/v)

Purpose

Antiseptic

Uses

Hand sanitizer to help reduce bacteria on the skin

Warnings

Flammable. Keep away from fire or flame.

When using this product

do not use in or near eyes. In case of contact, rinse eyes throughly with water

Stop use and ask a doctor if

If irritation or rash appears and lasts.

Keep out of reach of children

If swallowed, get medical help or contact a Poison Control Center

Directions

■ Dispense and rub onto hands until dry. Do not rinse off.

■ Children under 6 years of age should use this product under supervision.

Other information

■ Do not store above 110°F (43°C)

Inactive ingredients

Aloe Barbadensis (aloe vera) Leaf Juice, Aminomethyl Propanol, Butyrospermum Parkii (Shea) Butter, Carbomer, Glycerin, Isopropyl Myristate, Water (Aqua)